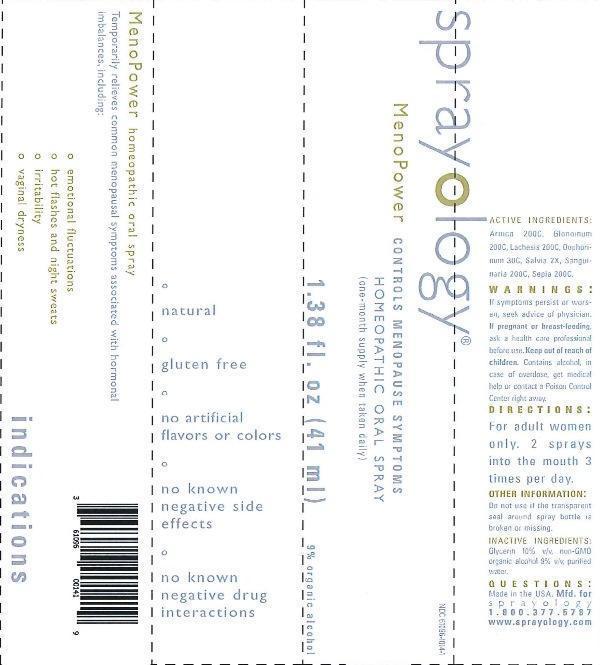 DRUG LABEL: Sprayology MenoPower
NDC: 61096-1014 | Form: LIQUID
Manufacturer: Eight and Company
Category: homeopathic | Type: HUMAN OTC DRUG LABEL
Date: 20160729

ACTIVE INGREDIENTS: ARNICA MONTANA 200 [hp_C]/41 mL; NITROGLYCERIN 200 [hp_C]/41 mL; LACHESIS MUTA VENOM 200 [hp_C]/41 mL; SUS SCROFA OVARY 30 [hp_C]/41 mL; SAGE 2 [hp_X]/41 mL; SANGUINARIA CANADENSIS ROOT 200 [hp_C]/41 mL; SEPIA OFFICINALIS JUICE 200 [hp_C]/41 mL
INACTIVE INGREDIENTS: GLYCERIN; ALCOHOL; WATER

Sprayology MenoPower

ACTIVE INGREDIENT

Active Ingredients: Arnica montana 200C, Glonoinum 200C, Lachesis mutus 200C, Oophorinum 30C, Salvia officinalis 2X, Sanguinaria canadensis 200C, Sepia 200C

WARNINGS

Warnings: If symptoms persist or worsen, seek advice of physician. If pregnant or breast-feeding, ask a health care professional before use. Keep out of reach of children. Contains alcohol, in case of overdose, get medical help or contact a Poison Control Center right away.

Keep out of reach of children.

Directions:

- For adult women only. 2 sprays into the mouth 3 times per day.

PURPOSE

Temporarily relieves common menopausal symptoms associated with hormonal imbalances, including:

- emotional fluctuations
- hot flashes and night sweats
- irritability
- vaginal dryness

Other Information: Do not use if the transparent seal around spray bottle is broken or missing.

INACTIVE INGREDIENT

Inactive Ingredients: Glycerin 10% v/v, non-GMO organic alcohol 9% v/v purified water.

INDICATIONS AND USAGE

Temporarily relieves common menopausal symptoms associated with hormonal imbalances, including:

° emotional fluctuations

° hot flashes and night sweats

° irritability

° vaginal dryness

° natural

° gluten free

° no artificial flavors or colors

° no known negative side effects

° no known negative drug interactions